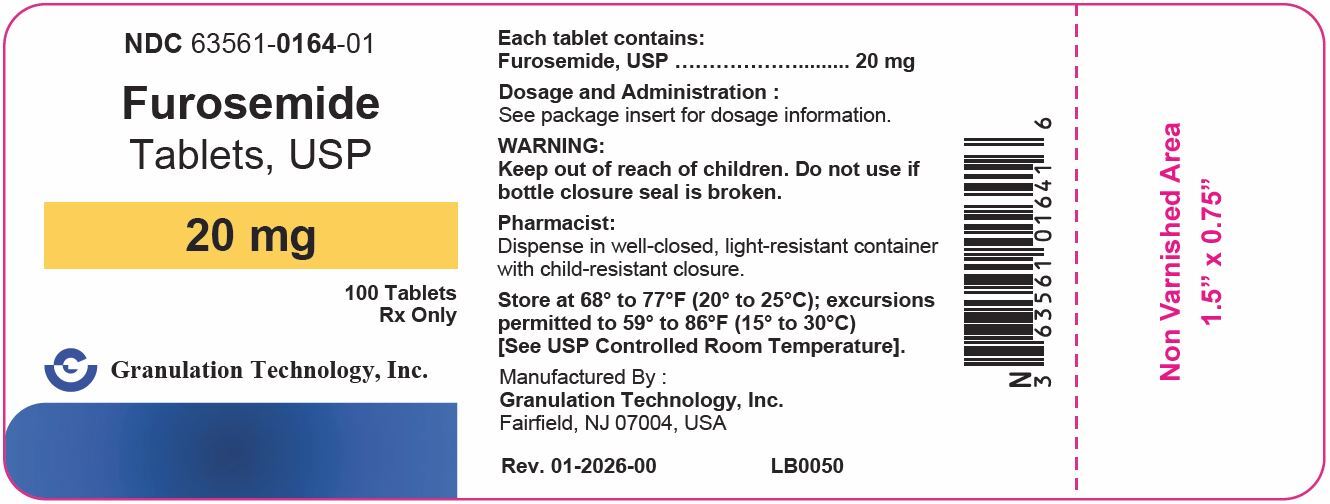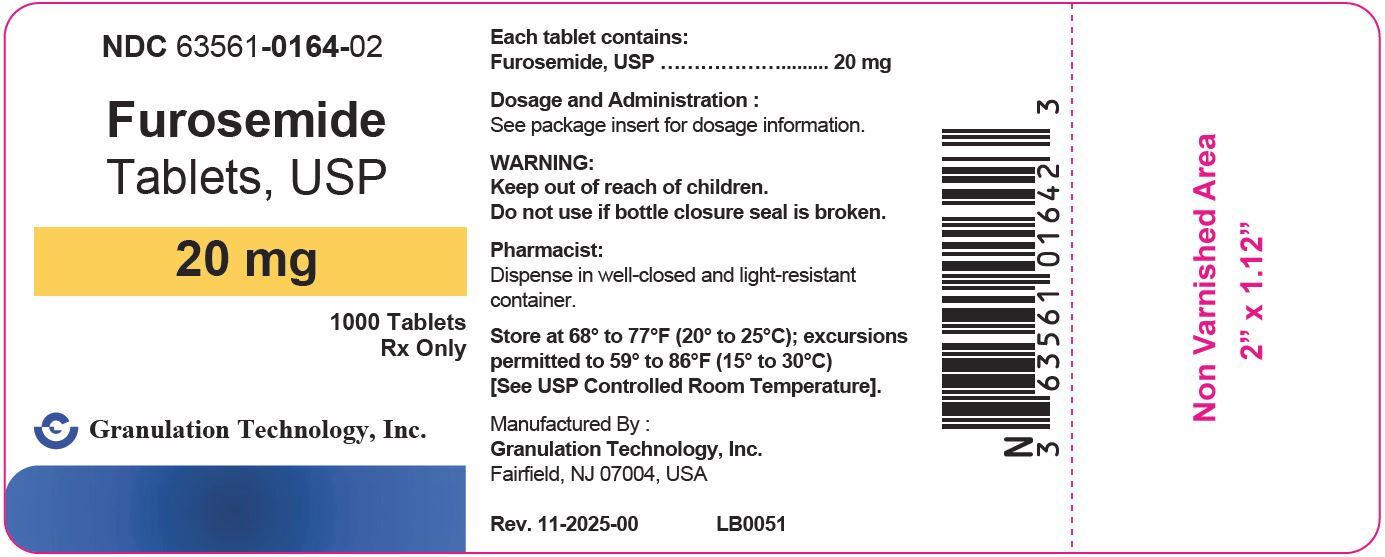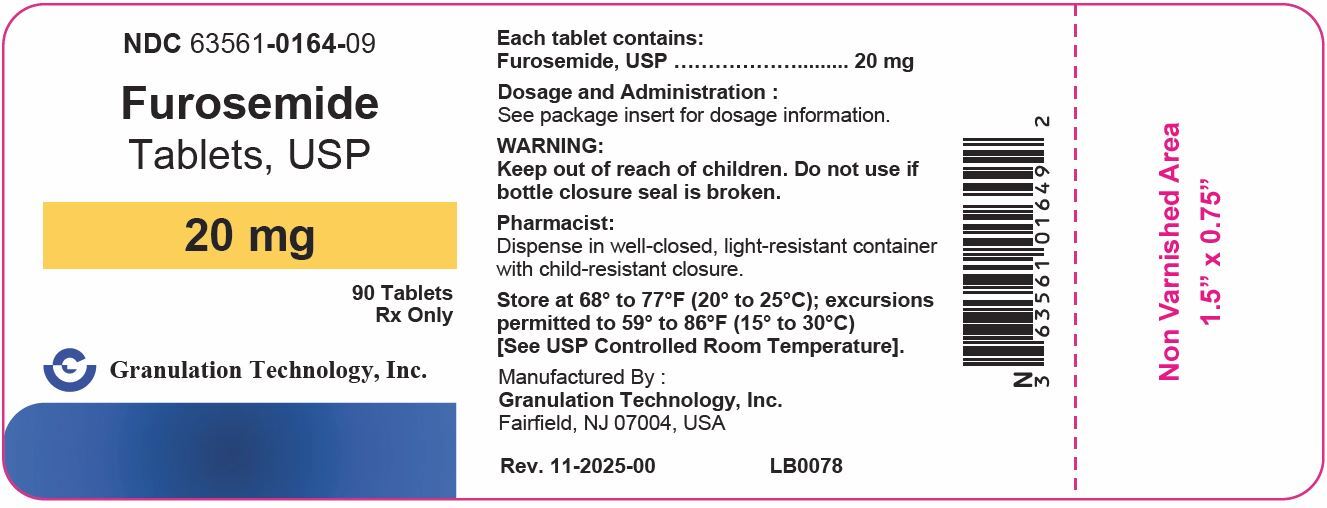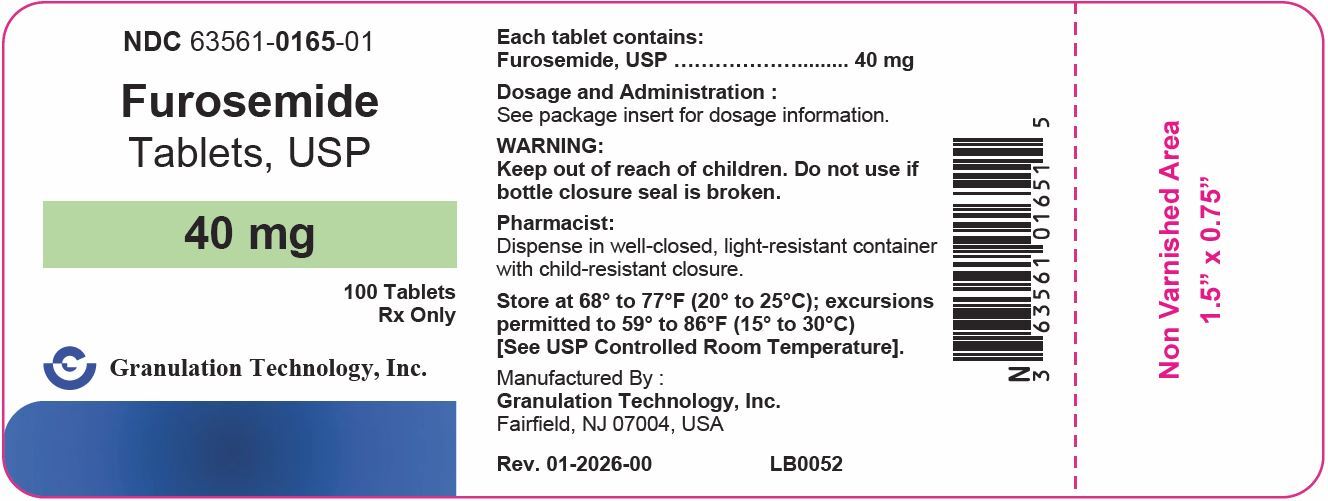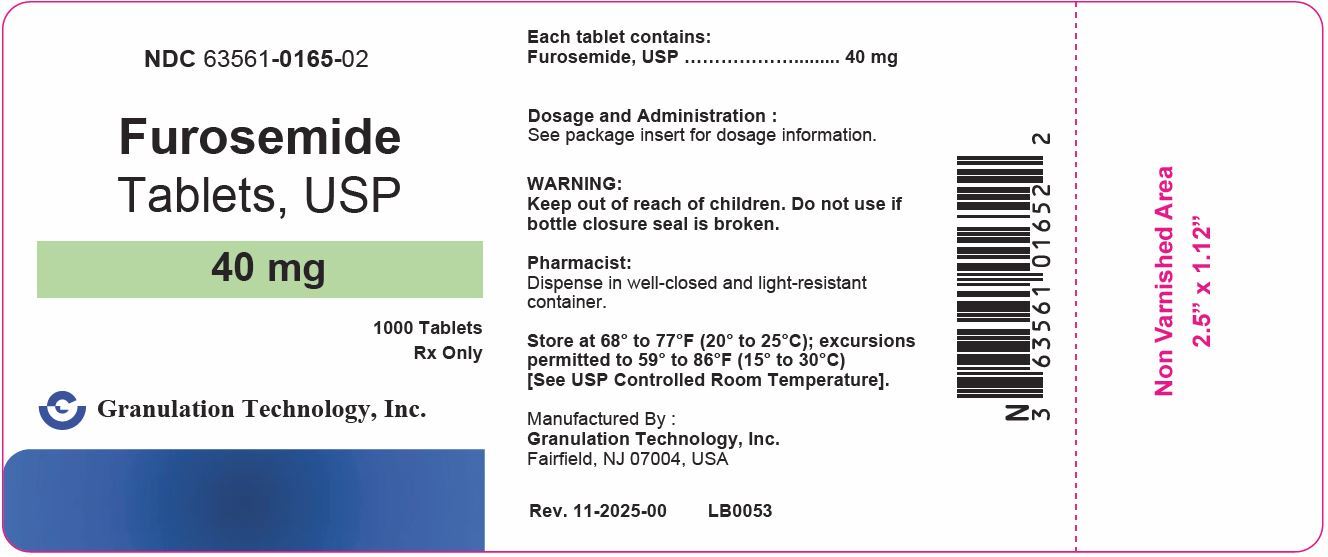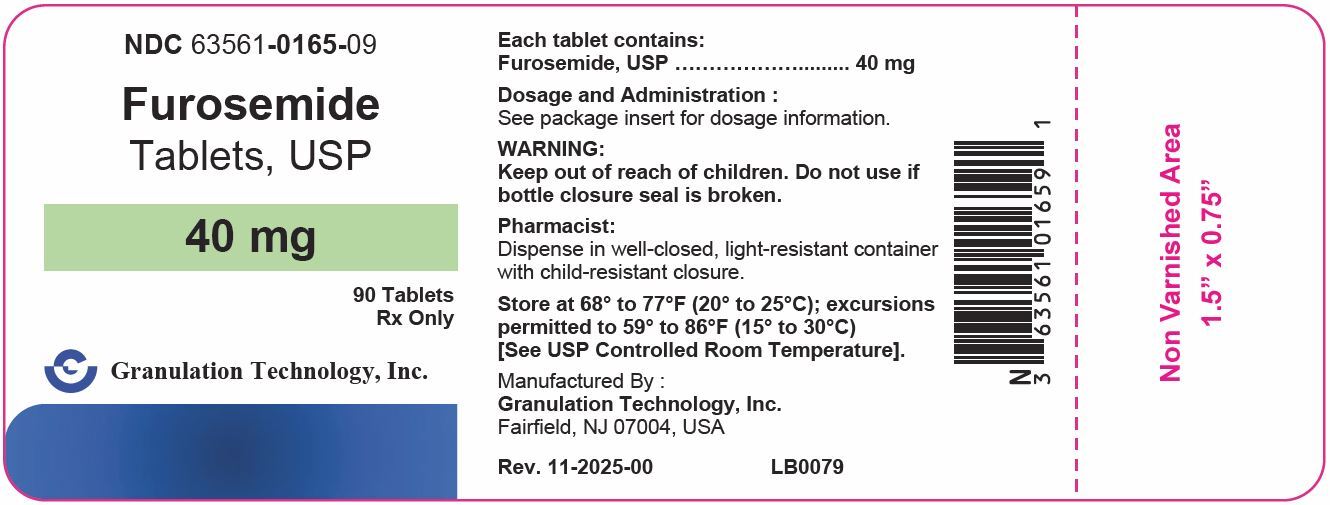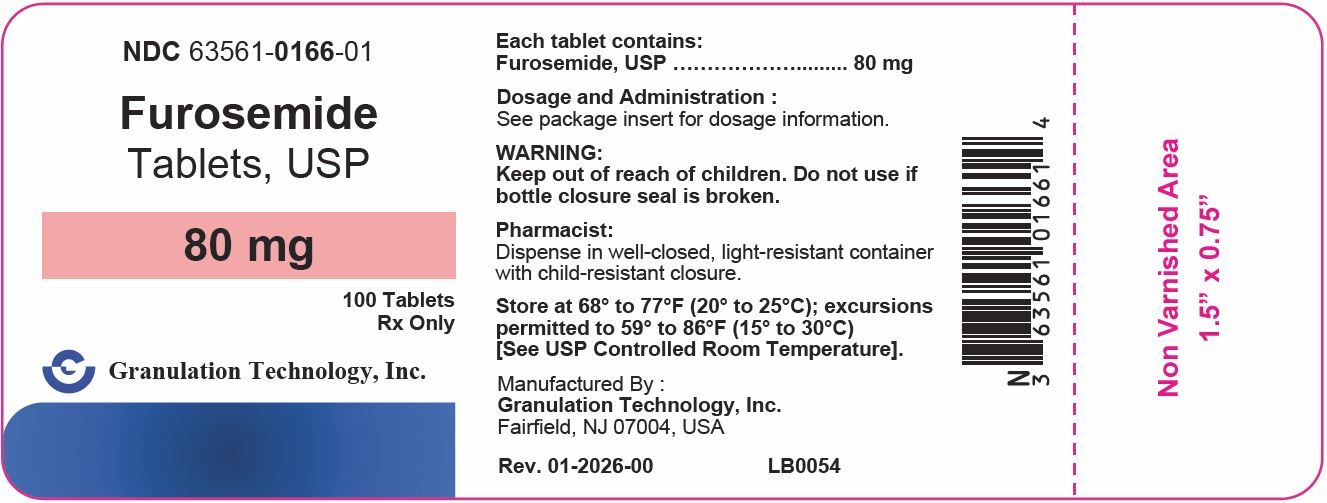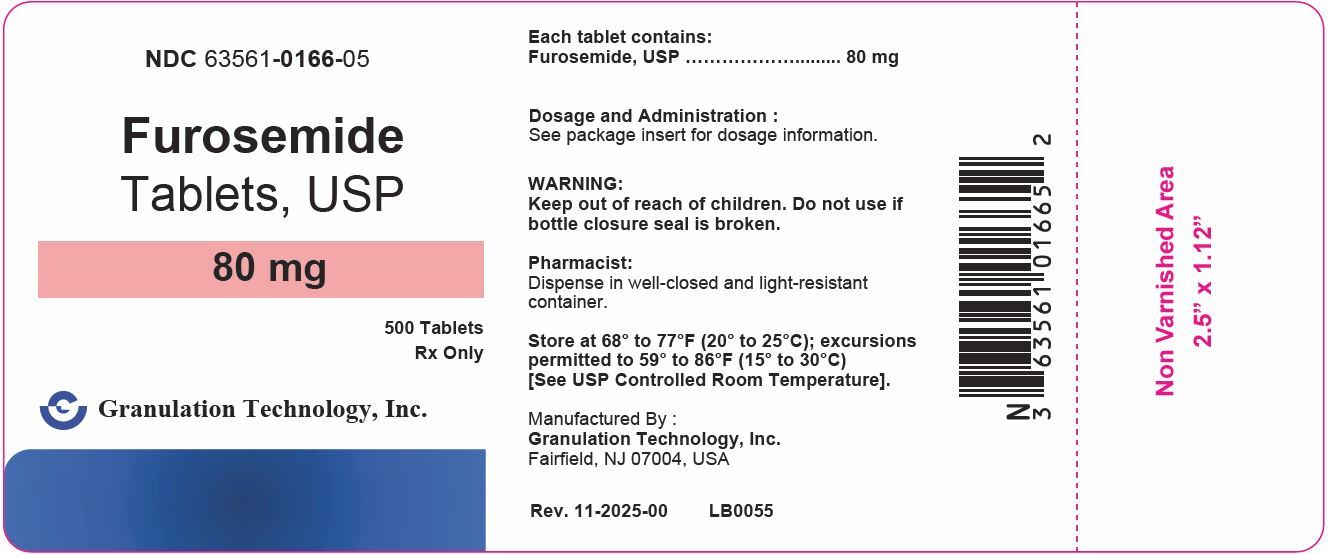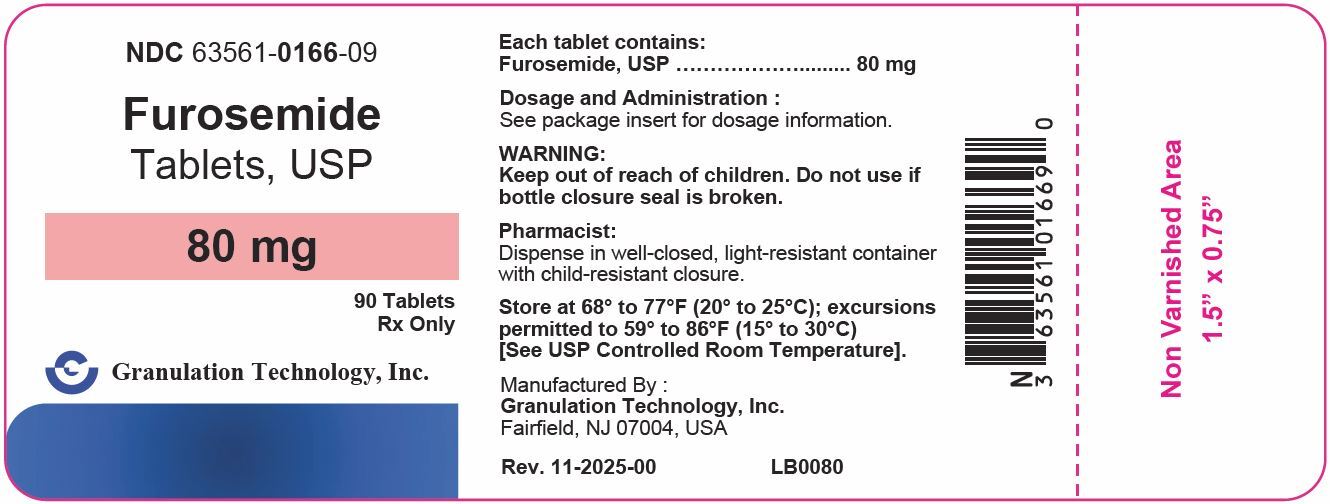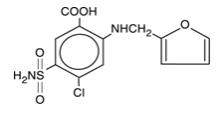 DRUG LABEL: Furosemide
NDC: 63561-0164 | Form: TABLET
Manufacturer: Granulation Technology, Inc.
Category: prescription | Type: HUMAN PRESCRIPTION DRUG LABEL
Date: 20260115

ACTIVE INGREDIENTS: FUROSEMIDE 20 mg/1 1
INACTIVE INGREDIENTS: LACTOSE MONOHYDRATE; MAGNESIUM STEARATE; STARCH, CORN

Furosemide Tablets, USP

Rx Only

WARNING

Furosemide is a potent diuretic which, if given in excessive amounts, can lead to a profound diuresis with water and electrolyte depletion. Therefore, careful medical supervision is required and dose and dose schedule must be adjusted to the individual patient’s needs [see DOSAGE AND ADMINISTRATION].

DESCRIPTION

Furosemide is a diuretic which is an anthranilic acid derivative. Chemically, it is 4-chloro- N-furfuryl-5-sulfamoylanthranilic acid. Furosemide is a white to off-white odorless crystalline powder. It is practically insoluble in water, sparingly soluble in alcohol, freely soluble in dilute alkali solutions and insoluble in dilute acids.

The structural formula is as follows:

Furosemide is available in 20 mg, 40 mg and 80 mg tablets for oral administration.

Inactive ingredients include lactose monohydrate, magnesium stearate, pregelatinized starch and starch (corn).

Meets USP Dissolution Test 1.

CLINICAL PHARMACOLOGY

Investigations into the mode of action of furosemide have utilized micropuncture studies in rats, stop flow experiments in dogs and various clearance studies in both humans and experimental animals. It has been demonstrated that furosemide inhibits primarily the absorption of sodium and chloride not only in the proximal and distal tubules but also in the loop of Henle. The high degree of efficacy is largely due to the unique site of action. The action on the distal tubule is independent of any inhibitory effect on carbonic anhydrase and aldosterone.

Recent evidence suggests that furosemide glucuronide is the only or at least the major biotransformation product of furosemide in man. Furosemide is extensively bound to plasma proteins, mainly to albumin. Plasma concentrations ranging from 1 to 400 mcg/mL are 91 to 99% bound in healthy individuals. The unbound fraction averages 2.3 to 4.1% at therapeutic concentrations.

The onset of diuresis following oral administration is within 1 hour. The peak effect occurs within the first or second hour. The duration of diuretic effect is 6 to 8 hours.

In fasted normal men, the mean bioavailability of furosemide from furosemide tablets and furosemide oral solution is 64% and 60%, respectively, of that from an intravenous injection of the drug. Although furosemide is more rapidly absorbed from the oral solution (50 minutes) than from the tablet (87 minutes), peak plasma levels and area under the plasma concentration-time curves do not differ significantly. Peak plasma concentrations increase with increasing dose but times-to-peak do not differ among doses. The terminal half-life of furosemide is approximately 2 hours.

Significantly more furosemide is excreted in urine following the IV injection than after the tablet or oral solution. There are no significant differences between the two oral formulations in the amount of unchanged drug excreted in urine.

Geriatric Population

Furosemide binding to albumin may be reduced in elderly patients. Furosemide is predominantly excreted unchanged in the urine. The renal clearance of furosemide after intravenous administration in older healthy male subjects (60 to 70 years of age) is statistically significantly smaller than in younger healthy male subjects (20 to 35 years of age). The initial diuretic effect of furosemide in older subjects is decreased relative to younger subjects [see PRECAUTIONS: Geriatric Use] .

INDICATIONS AND USAGE

Edema

Furosemide is indicated in adults and pediatric patients for the treatment of edema associated with congestive heart failure, cirrhosis of the liver, and renal disease, including the nephrotic syndrome. Furosemide is particularly useful when an agent with greater diuretic potential is desired.

Hypertension

Oral Furosemide may be used in adults for the treatment of hypertension alone or in combination with other antihypertensive agents. Hypertensive patients who cannot be adequately controlled with thiazides will probably also not be adequately controlled with Furosemide alone.

CONTRAINDICATIONS

Furosemide is contraindicated in patients with anuria and in patients with a history of hypersensitivity to furosemide.

WARNINGS

In patients with hepatic cirrhosis and ascites, Furosemide therapy is best initiated in the hospital. In hepatic coma and in states of electrolyte depletion, therapy should not be instituted until the basic condition is improved. Sudden alterations of fluid and electrolyte balance in patients with cirrhosis may precipitate hepatic coma; therefore, strict observation is necessary during the period of diuresis. Supplemental potassium chloride and, if required, an aldosterone antagonist are helpful in preventing hypokalemia and metabolic alkalosis.

If increasing azotemia and oliguria occur during treatment of severe progressive renal disease, Furosemide should be discontinued.

Cases of tinnitus and reversible or irreversible hearing impairment and deafness have been reported. Reports usually indicate that Furosemide ototoxicity is associated with rapid injection, severe renal impairment, the use of higher than recommended doses, hypoproteinemia or concomitant therapy with aminoglycoside antibiotics, ethacrynic acid, or other ototoxic drugs. If the physician elects to use high dose parenteral therapy, controlled intravenous infusion is advisable (for adults, an infusion rate not exceeding 4 mg Furosemide per minute has been used) [see PRECAUTIONS: Drug Interactions].

PRECAUTIONS

General

Excessive diuresis may cause dehydration and blood volume reduction with circulatory collapse and possibly vascular thrombosis and embolism, particularly in elderly patients. As with any effective diuretic, electrolyte depletion may occur during Furosemide therapy, especially in patients receiving higher doses and a restricted salt intake. Hypokalemia may develop with Furosemide, especially with brisk diuresis, inadequate oral electrolyte intake, when cirrhosis is present, or during concomitant use of corticosteroids, ACTH, licorice in large amounts, or prolonged use of laxatives. Digitalis therapy may exaggerate metabolic effects of hypokalemia, especially myocardial effects.

All patients receiving Furosemide therapy should be observed for these signs or symptoms of fluid or electrolyte imbalance (hyponatremia, hypochloremic alkalosis, hypokalemia, hypomagnesemia or hypocalcemia): dryness of mouth, thirst, weakness, lethargy, drowsiness, restlessness, muscle pains or cramps, muscular fatigue, hypotension, oliguria, tachycardia, arrhythmia, or gastrointestinal disturbances such as nausea and vomiting. Increases in blood glucose and alterations in glucose tolerance tests (with abnormalities of the fasting and 2-hour postprandial sugar) have been observed, and rarely, precipitation of diabetes mellitus has been reported.

In patients with severe symptoms of urinary retention (because of bladder emptying disorders, prostatic hyperplasia, urethral narrowing), the administration of furosemide can cause acute urinary retention related to increased production and retention of urine. Thus, these patients require careful monitoring, especially during the initial stages of treatment.

In patients at high risk for radiocontrast nephropathy, Furosemide can lead to a higher incidence of deterioration in renal function after receiving radiocontrast compared to high-risk patients who received only intravenous hydration prior to receiving radiocontrast.

In patients with hypoproteinemia (e.g., associated with nephrotic syndrome), the effect of Furosemide may be weakened and its ototoxicity potentiated.

Asymptomatic hyperuricemia can occur and gout may rarely be precipitated.

Patients allergic to sulfonamides may also be allergic to Furosemide. The possibility exists of exacerbation or activation of systemic lupus erythematosus.

As with many other drugs, patients should be observed regularly for the possible occurrence of blood dyscrasias, liver or kidney damage, or other idiosyncratic reactions.

Information for Patients

Patients receiving Furosemide should be advised that they may experience symptoms from excessive fluid and/or electrolyte losses. The postural hypotension that sometimes occurs can usually be managed by getting up slowly. Potassium supplements and/or dietary measures may be needed to control or avoid hypokalemia.

Patients with diabetes mellitus should be told that furosemide may increase blood glucose levels and thereby affect urine glucose tests. The skin of some patients may be more sensitive to the effects of sunlight while taking furosemide.

Hypertensive patients should avoid medications that may increase blood pressure, including over-the-counter products for appetite suppression and cold symptoms.

Laboratory Tests

Serum electrolytes (particularly potassium), CO2, creatinine and BUN should be determined frequently during the first few months of Furosemide therapy and periodically thereafter. Serum and urine electrolyte determinations are particularly important when the patient is vomiting profusely or receiving parenteral fluids. Abnormalities should be corrected or the drug temporarily withdrawn. Other medications may also influence serum electrolytes.

Reversible elevations of BUN may occur and are associated with dehydration, which should be avoided, particularly in patients with renal insufficiency.

Urine and blood glucose should be checked periodically in diabetics receiving Furosemide, even in those suspected of latent diabetes.

Furosemide may lower serum levels of calcium (rarely cases of tetany have been reported) and magnesium. Accordingly, serum levels of these electrolytes should be determined periodically.

In premature infants Furosemide may precipitate nephrocalcinosis/nephrolithiasis, therefore renal function must be monitored and renal ultrasonography performed [see PRECAUTIONS: Pediatric Use] .

Drug Interactions

Furosemide may increase the ototoxic potential of aminoglycoside antibiotics, especially in the presence of impaired renal function. Except in life-threatening situations, avoid this combination.

Furosemide should not be used concomitantly with ethacrynic acid because of the possibility of ototoxicity. Patients receiving high doses of salicylates concomitantly with Furosemide, as in rheumatic disease, may experience salicylate toxicity at lower doses because of competitive renal excretory sites.

There is a risk of ototoxic effects if cisplatin and Furosemide are given concomitantly. In addition, nephrotoxicity of nephrotoxic drugs such as cisplatin may be enhanced if Furosemide is not given in lower doses and with positive fluid balance when used to achieve forced diuresis during cisplatin treatment.

Furosemide has a tendency to antagonize the skeletal muscle-relaxing effect of tubocurarine and may potentiate the action of succinylcholine.

Lithium generally should not be given with diuretics because they reduce lithium’s renal clearance and add a high risk of lithium toxicity.

Furosemide combined with angiotensin-converting enzyme inhibitors or angiotensin II receptor blockers may lead to severe hypotension and deterioration in renal function, including renal failure. An interruption or reduction in the dosage of Furosemide, angiotensin-converting enzyme inhibitors, or angiotensin receptor blockers may be necessary.

Potentiation occurs with ganglionic or peripheral adrenergic blocking drugs.

Furosemide may decrease arterial responsiveness to norepinephrine. However, norepinephrine may still be used effectively.

Simultaneous administration of sucralfate and Furosemide tablets may reduce the natriuretic and antihypertensive effects ofFurosemide. Patients receiving both drugs should be observed closely to determine if the desired diuretic and/or antihypertensive effect of Furosemide is achieved. The intake of Furosemide and sucralfate should be separated by at least two hours.

In isolated cases, intravenous administration of Furosemide within 24 hours of taking chloral hydrate may lead to flushing, sweating attacks, restlessness, nausea, increase in blood pressure, and tachycardia. Use of Furosemide concomitantly with chloral hydrate is therefore not recommended.

Phenytoin interferes directly with renal action of Furosemide. There is evidence that treatment with phenytoin leads to decreased intestinal absorption of Furosemide, and consequently to lower peak serum furosemide concentrations.

Methotrexate and other drugs that, like Furosemide, undergo significant renal tubular secretion may reduce the effect of Furosemide. Conversely, Furosemide may decrease renal elimination of other drugs that undergo tubular secretion. High-dose treatment of both Furosemide and these other drugs may result in elevated serum levels of these drugs and may potentiate their toxicity as well as the toxicity of Furosemide.

Furosemide can increase the risk of cephalosporin-induced nephrotoxicity even in the setting of minor or transient renal impairment.

Concomitant use of cyclosporine and Furosemide is associated with increased risk of gouty arthritis secondary to Furosemide-induced hyperurecemia and cyclosporine impairment of renal urate excretion.

High doses (> 80 mg) of furosemide may inhibit the binding of thyroid hormones to carrier proteins and result in transient increase in free thyroid hormones, followed by an overall decrease in total thyroid hormone levels.

One study in six subjects demonstrated that the combination of furosemide and acetylsalicylic acid temporarily reduced creatinine clearance in patients with chronic renal insufficiency. There are case reports of patients who developed increased BUN, serum creatinine and serum potassium levels, and weight gain when furosemide was used in conjunction with NSAIDs.

Literature reports indicate that coadministration of indomethacin may reduce the natriuretic and antihypertensive effects of Furosemide in some patients by inhibiting prostaglandin synthesis. Indomethacin may also affect plasma renin levels, aldosterone excretion, and renin profile evaluation. Patients receiving both indomethacin and Furosemide should be observed closely to determine if the desired diuretic and/or antihypertensive effect of Furosemide is achieved.

Carcinogenesis, Mutagenesis, Impairment of Fertility

Furosemide was tested for carcinogenicity by oral administration in one strain of mice and one strain of rats. A small but significantly increased incidence of mammary gland carcinomas occurred in female mice at a dose 17.5 times the maximum human dose of 600 mg. There were marginal increases in uncommon tumors in male rats at a dose of 15 mg/kg (slightly greater than the maximum human dose) but not at 30 mg/kg.

Furosemide was devoid of mutagenic activity in various strains of Salmonella typhimurium when tested in the presence or absence of an in vitro metabolic activation system, and questionably positive for gene mutation in mouse lymphoma cells in the presence of rat liver S9 at the highest dose tested. Furosemide did not induce sister chromatid exchange in human cells in vitro, but other studies on chromosomal aberrations in human cells in vitro gave conflicting results. In Chinese hamster cells it induced chromosomal damage but was questionably positive for sister chromatid exchange. Studies on the induction by furosemide of chromosomal aberrations in mice were inconclusive. The urine of rats treated with this drug did not induce gene conversion in Saccharomyces cerevisiae.

Furosemide produced no impairment of fertility in male or female rats, at 100 mg/kg/day (the maximum effective diuretic dose in the rat and 8 times the maximal human dose of 600 mg/day).

Pregnancy

Furosemide has been shown to cause unexplained maternal deaths and abortions in rabbits at 2, 4 and 8 times the maximal recommended human dose. There are no adequate and well-controlled studies in pregnant women. Furosemide should be used during pregnancy only if the potential benefit justifies the potential risk to the fetus.

Treatment during pregnancy requires monitoring of fetal growth because of the potential for higher birth weights.

The effects of furosemide on embryonic and fetal development and on pregnant dams were studied in mice, rats and rabbits.

Furosemide caused unexplained maternal deaths and abortions in the rabbit at the lowest dose of 25 mg/kg (2 times the maximal recommended human dose of 600 mg/day). In another study, a dose of 50 mg/kg (4 times the maximal recommended human dose of 600 mg/day) also caused maternal deaths and abortions when administered to rabbits between Days 12 and 17 of gestation. In a third study, none of the pregnant rabbits survived a dose of 100 mg/kg. Data from the above studies indicate fetal lethality that can precede maternal deaths.

The results of the mouse study and one of the three rabbit studies also showed an increased incidence and severity of hydronephrosis (distention of the renal pelvis and, in some cases, of the ureters) in fetuses derived from the treated dams as compared with the incidence in fetuses from the control group.

Nursing Mothers

Because it appears in breast milk, caution should be exercised when Furosemide is administered to a nursing mother.

Furosemide may inhibit lactation.

Pediatric Use

In premature infants Furosemide may precipitate nephrocalcinosis/nephrolithiasis.

Nephrocalcinosis/nephrolithiasis has also been observed in children under 4 years of age with no history of prematurity who have been treated chronically with Furosemide. Monitor renal function, and renal ultrasonography should be considered, in pediatric patients receiving Furosemide.

If Furosemide is administered to premature infants during the first weeks of life, it may increase the risk of persistence of patent ductus arteriosus.

Geriatric Use

Controlled clinical studies of Furosemide did not include sufficient numbers of subjects aged 65 and over to determine whether they respond differently from younger subjects. Other reported clinical experience has not identified differences in responses between the elderly and younger patients. In general, dose selection for the elderly patient should be cautious, usually starting at the low end of the dosing range, reflecting the greater frequency of decreased hepatic, renal, or cardiac function, and of concomitant disease or other drug therapy.

This drug is known to be substantially excreted by the kidney, and the risk of toxic reactions to this drug may be greater in patients with impaired renal function. Because elderly patients are more likely to have decreased renal function, care should be taken in dose selection and it may be useful to monitor renal function [see PRECAUTIONS: Generaland DOSAGE AND ADMINISTRATION] .

ADVERSE REACTIONS

Adverse reactions are categorized below by organ system and listed by decreasing severity.

Gastrointestinal System Reactions

1. hepatic encephalopathy in patients with hepatocellular insufficiency
2. pancreatitis
3. jaundice (intrahepatic cholestatic jaundice)
4. increased liver enzymes
5. anorexia
6. oral and gastric irritation
7. cramping
8. diarrhea
9. constipation
10. nausea
11. vomiting

Systemic Hypersensitivity Reactions

1. severe anaphylactic or anaphylactoid reactions (e.g., with shock)
2. systemic vasculitis
3. interstitial nephritis
4. necrotizing angiitis

Central Nervous System Reactions

1. tinnitus and hearing loss
2. paresthesias
3. vertigo
4. dizziness
5. headache
6. blurred vision
7. xanthopsia

Hematologic Reactions

1. aplastic anemia
2. thrombocytopenia
3. agranulocytosis
4. hemolytic anemia
5. leukopenia
6. anemia
7. eosinophilia

Dermatologic-Hypersensitivity Reactions

1. toxic epidermal necrolysis
2. Stevens-Johnson Syndrome
3. erythema multiforme
4. drug rash with eosinophilia and systemic symptoms
5. acute generalized exanthematous pustulosis
6. exfoliative dermatitis
7. bullous pemphigoid
8. purpura
9. photosensitivity
10. rash
11. pruritis
12. urticaria

Cardiovascular Reaction

1. Orthostatic hypotension may occur and be aggravated by alcohol, barbiturates, or narcotics.
2. Increase in cholesterol and triglyceride serum levels.

Other Reactions

1. hyperglycemia
2. glycosuria
3. hyperuricemia
4. muscle spasm
5. weakness
6. restlessness
7. urinary bladder spasm
8. thrombophlebitis
9. fever

Whenever adverse reactions are moderate or severe, Furosemide dosage should be reduced or therapy withdrawn. To report SUSPECTED ADVERSE REACTIONS, contact Granulation Technology, Inc. at 1-973-276-0740 or FDA at 1-800-FDA-1088 or www.fda.gov/medwatch.

OVERDOSAGE

The principal signs and symptoms of overdose with Furosemide are dehydration, blood volume reduction, hypotension, electrolyte imbalance, hypokalemia and hypochloremic alkalosis, and are extensions of its diuretic action.

The acute toxicity of Furosemide has been determined in mice, rats and dogs. In all three, the oral LD50 exceeded 1000 mg/kg body weight, while the intravenous LD50 ranged from 300 to 680 mg/kg. The acute intragastric toxicity in neonatal rats is 7 to 10 times that of adult rats.

The concentration of Furosemide in biological fluids associated with toxicity or death is not known.

Treatment of overdosage is supportive and consists of replacement of excessive fluid and electrolyte losses. Serum electrolytes, carbon dioxide level and blood pressure should be determined frequently. Adequate drainage must be assured in patients with urinary bladder outlet obstruction (such as prostatic hypertrophy).

Hemodialysis does not accelerate furosemide elimination.

DOSAGE AND ADMINISTRATION

Edema

Therapy should be individualized according to patient response to gain maximal therapeutic response and to determine the minimal dose needed to maintain that response.

Adults

The usual initial dose of Furosemide is 20 mg to 80 mg given as a single dose. Ordinarily a prompt diuresis ensues. If needed, the same dose can be administered 6 to 8 hours later or the dose may be increased. The dose may be raised by 20 mg or 40 mg and given not sooner than 6 to 8 hours after the previous dose until the desired diuretic effect has been obtained. The individually determined single dose should then be given once or twice daily (e.g., at 8 am and 2 pm). The dose of Furosemide may be carefully titrated up to 600 mg/day in patients with clinically severe edematous states.

Edema may be most efficiently and safely mobilized by giving Furosemide on 2 to 4 consecutive days each week.

When doses exceeding 80 mg/day are given for prolonged periods, careful clinical observation and laboratory monitoring are particularly advisable [see PRECAUTIONS: Laboratory Test].

Geriatric Patients

In general, dose selection for the elderly patient should be cautious, usually starting at the low end of the dosing range [see PRECAUTIONS: Geriatric Use] .

Pediatric Patients

The usual initial dose of oral Furosemide in pediatric patients is 2 mg/kg body weight, given as a single dose. If the diuretic response is not satisfactory after the initial dose, dosage may be increased by 1 or 2 mg/kg no sooner than 6 to 8 hours after the previous dose. Doses greater than 6 mg/kg body weight are not recommended. For maintenance therapy in pediatric patients, the dose should be adjusted to the minimum effective level.

Hypertension

Therapy should be individualized according to the patient’s response to gain maximal therapeutic response and to determine the minimal dose needed to maintain the therapeutic response.

Adults

The usual initial dose of Furosemide for hypertension is 80 mg, usually divided into 40 mg twice a day. Dosage should then be adjusted according to response. If response is not satisfactory, add other antihypertensive agents.

Changes in blood pressure must be carefully monitored when Furosemide is used with other antihypertensive drugs, especially during initial therapy. To prevent excessive drop in blood pressure, the dosage of other agents should be reduced by at least 50% when Furosemide is added to the regimen. As the blood pressure falls under the potentiating effect of Furosemide, a further reduction in dosage or even discontinuation of other antihypertensive drugs may be necessary.

Geriatric Patients

In general, dose selection and dose adjustment for the elderly patient should be cautious, usually starting at the low end of the dosing range [see PRECAUTIONS: Geriatric Use] .

HOW SUPPLIED

Furosemide tablets, USP, for oral administration, are available as:

20 mg: White to off-white, round, flat face, radius edge, debossed “G 164” on one side and plain on the other side, and supplied as:

NDC 63561-0164-09 bottles of 90

NDC 63561-0164-01 bottles of 100

NDC 63561-0164-02 bottles of 1000

40 mg: White to off-white, round, flat face, radius edge, scored tablet debossed “G” above the score and “165” below the score on one side and plain on the other side, and supplied as:

NDC 63561-0165-09 bottles of 90

NDC 63561-0165-01 bottles of 100

NDC 63561-0165-02 bottles of 1000

80 mg: White to off-white, round, flat face, radius edge, scored tablet debossed “G” above the score and “166” below the score on one side and plain on the other side, and supplied as:

NDC 63561-0166-09 bottles of 90

NDC 63561-0166-01 bottles of 100

NDC 63561-0166-05 bottles of 500

Dispense in well-closed and light-resistant containers. Exposure to light might cause a slight discoloration. Discolored tablets should not be dispensed.

Store at 68º to 77ºF (20º to 25ºC); excursions permitted to 59º to 86ºF (15º to 30ºC) [See USP Controlled Room Temperature].

Manufactured by

Granulation Technology, Inc.
Fairfield, NJ 07004

Rev. January 2026

PRINCIPAL DISPLAY PANEL

NDC 63561-0164-09

Furosemide Tablets, USP 20 mg

90 Tablets
Rx Only

NDC 63561-0164-01

Furosemide Tablets, USP 20 mg

100 Tablets
Rx Only

NDC 63561-0164-02

Furosemide Tablets, USP 20 mg

1000 Tablets

Rx Only

PRINCIPAL DISPLAY PANEL

NDC 63561-0165-09

Furosemide Tablets, USP 40 mg

90 Tablets
Rx Only

NDC 63561-0165-01

Furosemide Tablets, USP 40 mg

100 Tablets
Rx Only

NDC 63561-0165-02

Furosemide Tablets, USP 40 mg

1000 Tablets
Rx Only

PRINCIPAL DISPLAY PANEL

NDC 63561-0166-09

Furosemide Tablets, USP 80 mg

90 Tablets
Rx Only

NDC 63561-0166-01

Furosemide Tablets, USP 80 mg

100 Tablets
Rx Only

NDC 63561-0166-05

Furosemide Tablets, USP 80 mg

500 Tablets
Rx Only